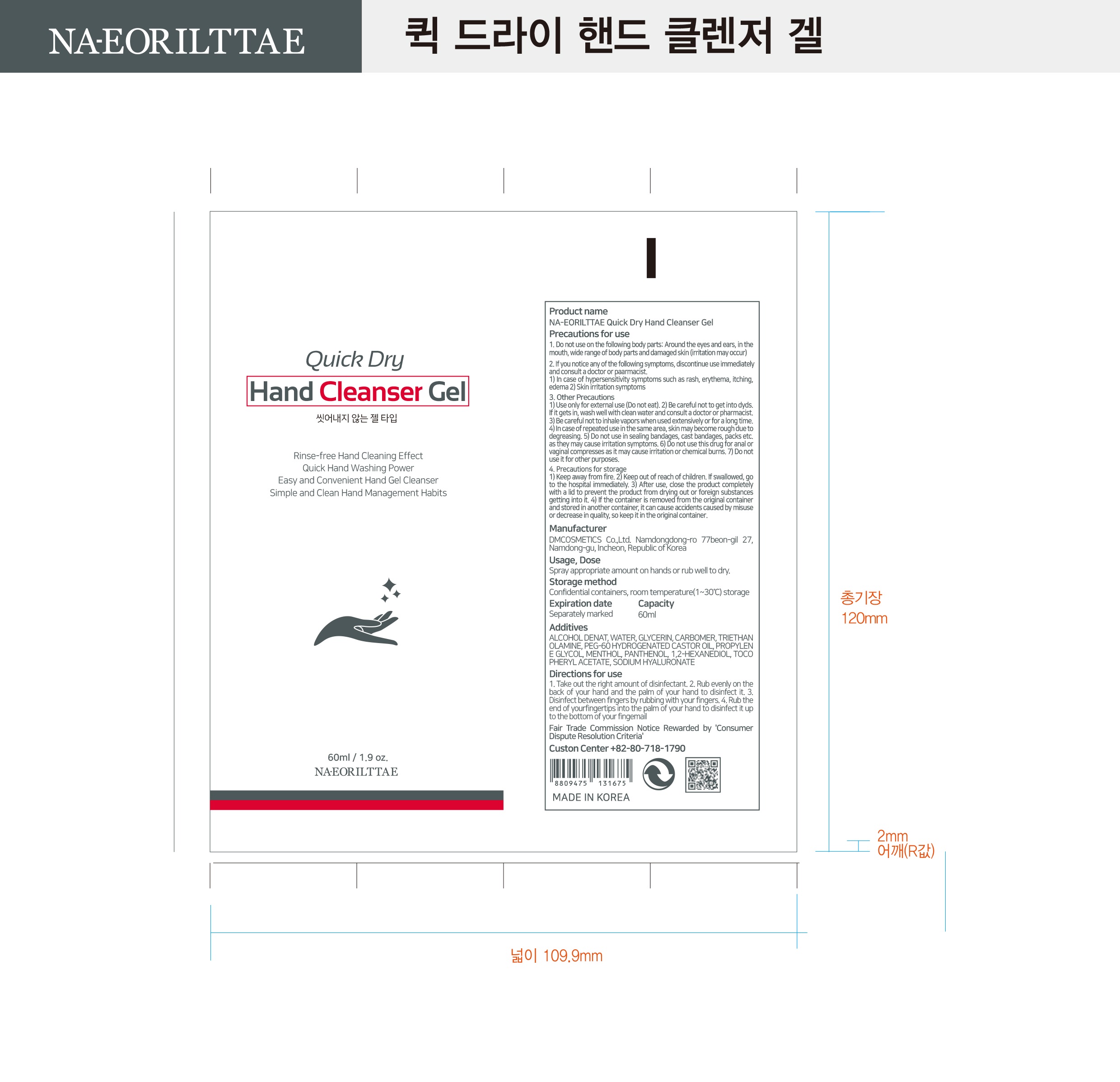 DRUG LABEL: NA-EORILTTAE Quick Dry Hand Cleanser gel
NDC: 77930-0011 | Form: GEL
Manufacturer: DM COSMETICS CO LTD
Category: otc | Type: HUMAN OTC DRUG LABEL
Date: 20200516

ACTIVE INGREDIENTS: ALCOHOL 63.16 mL/100 mL
INACTIVE INGREDIENTS: .ALPHA.-TOCOPHEROL ACETATE; GLYCERIN; PROPYLENE GLYCOL; PEG-60 HYDROGENATED CASTOR OIL; MENTHOL; PANTHENOL; 1,2-HEXANEDIOL; CARBOMER 940; TROLAMINE; WATER; HYALURONATE SODIUM

Drug Facts

ACTIVE INGREDIENT

alcohol

INACTIVE INGREDIENT

WATER
GLYCERIN
CARBOMER
TRIETHANOLAMINE
PEG-60 HYDROGENATED CASTOR OIL
PROPYLENE GLYCOL
MENTHOL
PANTHENOL
1,2-HEXANEDIOL
TOCOPHERYL ACETATE
SODIUM HYALURONATE

PURPOSE

Sterilization of hands

KEEP OUT OF REACH OF THE CHILDREN

INDICATIONS AND USAGE

Apply to clean, dry hands. Apply sufficient amount to thoroughly wet all surfaces of hands and fingers. Rub onto hands until dry.

Supervise children in the use of this product.

WARNINGS

■ For external use only.

■ Do not use in eyes.

■ lf swallowed, get medical help promptly.

■ Stop use, ask doctor lf irritation occurs.

■ Keep out of reach of children.

DOSAGE AND ADMINISTRATION

for external use only